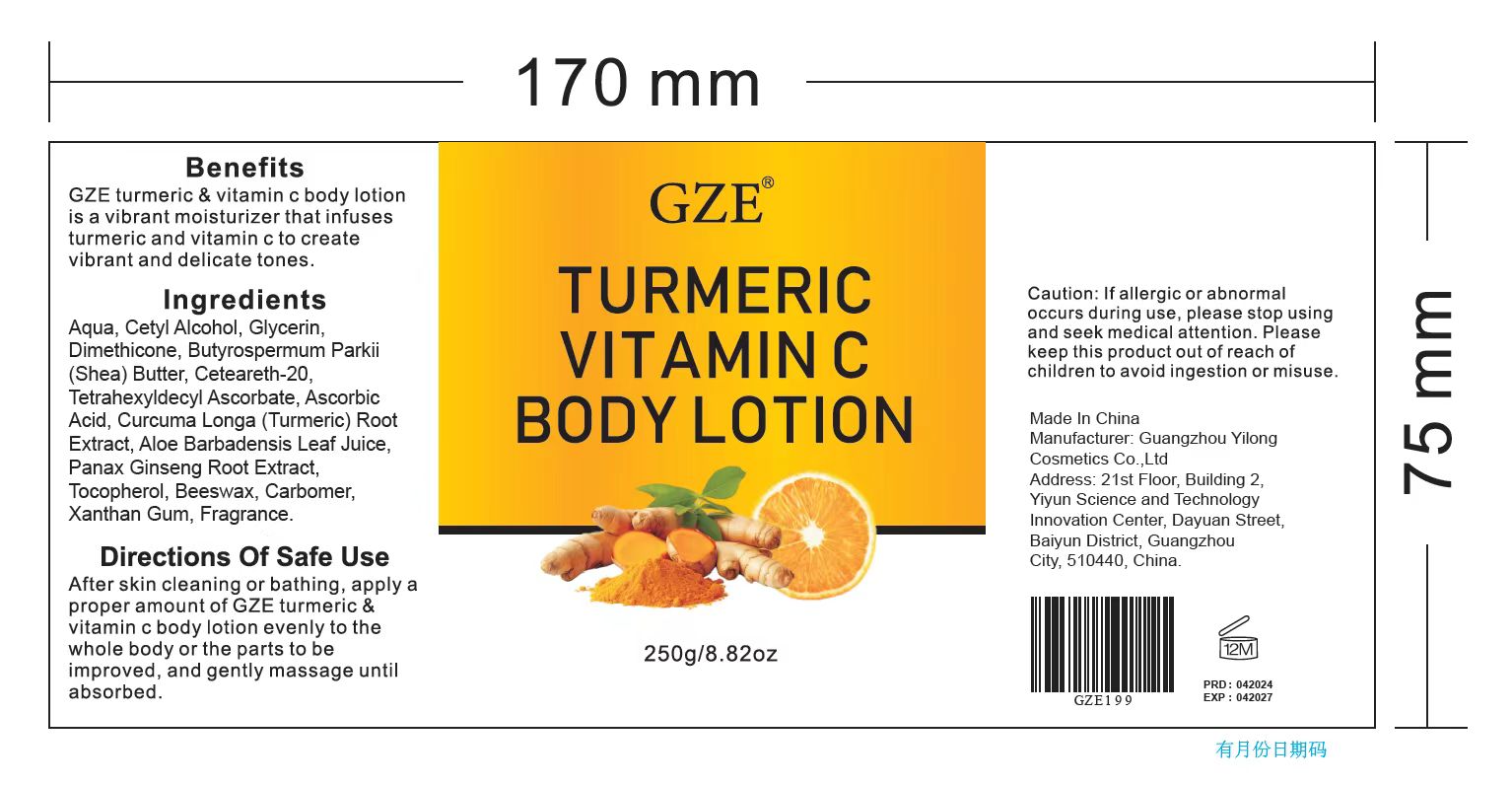 DRUG LABEL: GZE Turmeric Vitamin C BodyLotion
NDC: 74458-199 | Form: LOTION
Manufacturer: Guangzhou Yilong Cosmetics Co., Ltd
Category: otc | Type: HUMAN OTC DRUG LABEL
Date: 20241025

ACTIVE INGREDIENTS: CURCUMA LONGA (TURMERIC) ROOT EXTRACT 2 g/100 g; ASCORBIC ACID 2 g/100 g; TETRAHEXYLDECYL ASCORBATE 2 g/100 g
INACTIVE INGREDIENTS: DIMETHICONE; CETEARETH-20; CETYL ALCOHOL; TOCOPHEROL; GLYCERIN; ALOE BARBADENSIS LEAF JUICE; CARBOMER; BUTYROSPERMUM PARKII (SHEA) BUTTER; PANAX GINSENG ROOT; BEESWAX; AQUA; XANTHAN GUM

GZE TURMERIC VITAMIN C BODY LOTION

ACTIVE INGREDIENT

Tetrahexyldecyl Ascorbate

2%

Ascorbic Acid

2%

Curcuma Longa (Turmeric) Root Extract

2%

PURPOSE

Brightens skin tone.

INDICATIONS AND USAGE

After skin cleaning or bathing, apply a proper amount of GZE turmeric & vitamin c body lotion evenly to the whole body or the parts to be improved, and gently massage untl it absorbed.

WARNINGS

For external use only.

Stop use and ask a doctor if rash occurs.

Do not use on damaged or broken skin.

When using this product keep out of eyes. Rinse with water to remove.

Keep out of reach of children. If swallowed, get medical help or contact a Poison Control Center right away.

DOSAGE AND ADMINISTRATION

After skin cleaning or bathing, apply a proper amount of GZE turmeric & vitamin c body lotion evenly to the whole body or the parts to be improved, and gently massage untl it absorbed.

INACTIVE INGREDIENT

Aqua

Cetyl Alcohol

Glycerin

Dimethicone

Butyrospermum Parkii (Shea) Butter

Ceteareth-20

Aloe Barbadensis Leaf Juice

Panax Ginseng Root Extract

Tocopherol

Beeswax

Carbomer

Xanthan Gum

Fragrance